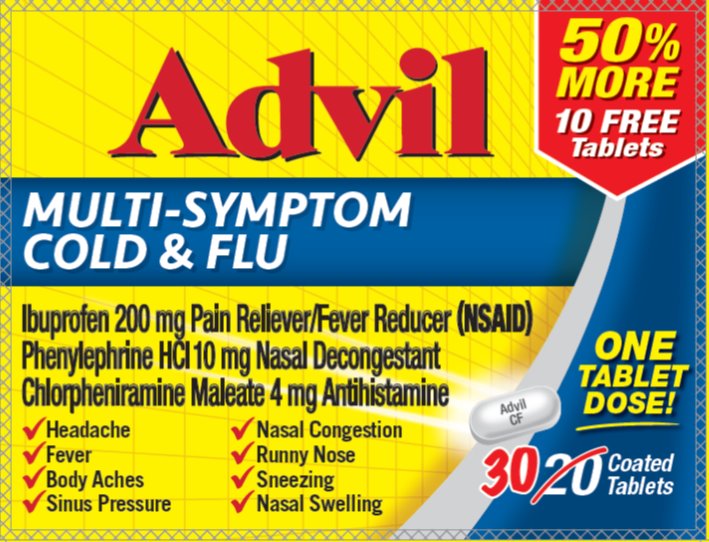 DRUG LABEL: Advil Multi-Symptom Cold and Flu
NDC: 0573-0190 | Form: TABLET, COATED
Manufacturer: Haleon US Holdings LLC
Category: otc | Type: HUMAN OTC DRUG LABEL
Date: 20251003

ACTIVE INGREDIENTS: CHLORPHENIRAMINE MALEATE 4 mg/1 1; IBUPROFEN 200 mg/1 1; PHENYLEPHRINE HYDROCHLORIDE 10 mg/1 1
INACTIVE INGREDIENTS: ACESULFAME POTASSIUM; CARNAUBA WAX; SILICON DIOXIDE; CROSCARMELLOSE SODIUM; GLYCERIN; GLYCERYL DIBEHENATE; HYPROMELLOSE, UNSPECIFIED; LACTIC ACID, UNSPECIFIED FORM; SOYBEAN LECITHIN; MALTODEXTRIN; MEDIUM-CHAIN TRIGLYCERIDES; MICROCRYSTALLINE CELLULOSE; POLYDEXTROSE; POLYVINYL ALCOHOL, UNSPECIFIED; PROPYL GALLATE; SUCRALOSE; TALC; TITANIUM DIOXIDE; TRIACETIN; XANTHAN GUM; STARCH, CORN; FERRIC OXIDE RED

Advil MultiSymptom Cold and Flu NDC 0573-0190

Active ingredients (in each tablet)

Chlorpheniramine maleate 4 mg

Ibuprofen 200 mg (NSAID)*

Phenylephrine HCl 10 mg

*nonsteroidal anti-inflammatory drug

Purposes

Antihistamine

Pain reliever/Fever reducer

Nasal decongestant

Uses

- temporarily relieves these symptoms associated with the common cold or flu:
  - headache
  - fever
  - minor body aches and pains
  - nasal congestion
  - runny nose
  - sinus pressure
  - sneezing
- reduces swelling of the nasal passages
- temporarily restores freer breathing through the nose

Warnings

Allergy alert: Ibuprofen may cause a severe allergic reaction, especially in people allergic to aspirin. Symptoms may include:

- hives
- facial swelling
- asthma (wheezing)
- shock
- skin reddening
- rash
- blisters

If an allergic reaction occurs, stop use and seek medical help right away.

Stomach bleeding warning: This product contains an NSAID, which may cause severe stomach bleeding. The chance is higher if you:

- are age 60 or older
- have had stomach ulcers or bleeding problems
- take a blood thinning (anticoagulant) or steroid drug
- take other drugs containing prescription or nonprescription NSAIDs [aspirin, ibuprofen, naproxen, or others]
- have 3 or more alcoholic drinks every day while using this product
- take more or for a longer time than directed

Do not use

- in children under 12 years of age
- if you have ever had an allergic reaction to any other pain reliever/fever reducer
- right before or after heart surgery
- if you are now taking a prescription monoamine oxidase inhibitor (MAOI) (certain drugs for depression, psychiatric, or emotional conditions, or Parkinson's disease), or for 2 weeks after stopping the MAOI drug. If you do not know if your prescription drug contains an MAOI, ask a doctor or pharmacist before taking this product.

Ask a doctor before use if

- you have a breathing problem such as emphysema or chronic bronchitis
- stomach bleeding warning applies to you
- you have problems or serious side effects from taking pain relievers or fever reducers
- you have a history of stomach problems, such as heartburn
- you have high blood pressure, heart disease, liver cirrhosis, kidney disease, asthma, thyroid disease, diabetes, glaucoma, have trouble urinating due to an enlarged prostate gland, or had a stroke
- you are taking a diuretic

Ask a doctor or pharmacist before use if you are

- under a doctor's care for any serious condition
- taking sedatives or tranquilizers
- taking any other product that contains phenylephrine, chlorpheniramine or any other nasal decongestant or antihistamine
- taking aspirin for heart attack or stroke, because ibuprofen may decrease this benefit of aspirin
- taking any other drug

When using this product

- take with food or milk if stomach upset occurs
- avoid alcoholic drinks
- be careful when driving a motor vehicle or operating machinery
- drowsiness may occur
- alcohol, sedatives, and tranquilizers may increase drowsiness
- may cause excitability especially in children

Stop use and ask a doctor if

- you experience any of the following signs of stomach bleeding:
  - feel faint
  - vomit blood
  - have bloody or black stools
  - have stomach pain that does not get better
- you have symptoms of heart problems or stroke:
  - chest pain
  - trouble breathing
  - weakness in one part or side of body
  - slurred speech
  - leg swelling
- pain gets worse or lasts more than 7 days
- fever gets worse or lasts more than 3 days
- nasal congestion lasts for more than 7 days
- redness or swelling is present in the painful area
- you get nervous, dizzy, or sleepless
- symptoms continue or get worse
- any new symptoms appear

PREGNANCY OR BREAST FEEDING

If pregnant or breast-feeding,ask a health professional before use. It is especially important not to use ibuprofen at 20 weeks or later in pregnancy unless definitely directed to do so by a doctor because it may cause problems in the unborn child or complications during delivery.

Keep out of reach of children.In case of overdose, get medical help or contact a Poison Control Center right away.

Directions

- do not take more than directed
- adults and children 12 years of age and over:
  - take 1 tablet every 4 hours while symptoms persist
  - do not take more than 6 tablets in any 24-hour period, unless directed by a doctor
- children under 12 years of age: do not use

Other information

- read all warnings and directions before use. Keep carton.
- store at 20-25°C (68-77°F)
- avoid excessive heat above 40°C (104°F)

Inactive ingredients

acesulfame potassium, artificial flavors, carnauba wax, colloidal silicon dioxide, corn starch, croscarmellose sodium, glycerin, glyceryl dibehenate, hypromellose, lactic acid, lecithin, maltodextrin, medium-chain triglycerides, microcrystalline cellulose, pharmaceutical ink, polydextrose, polyvinyl alcohol, pregelatinized starch, propyl gallate, silicon dioxide, sucralose, synthetic iron oxide, talc, titanium dioxide, triacetin, xanthan gum

Questions or comments?Call weekdays from 9 AM to 5 PM ESTtoll free at 1-800-88-ADVIL

Additional Information

READ AND KEEP CARTON FOR COMPLETE
WARNINGS AND INFORMATION

Product inside sealed in plastic blister with foil backing.
Do Not Use if plastic blister or foil barrier is broken.

Distributed by: GSK Consumer Healthcare, Warren, NJ 07059

For most recent product information,

visit www.advil.com

Trademarks owned or licensed by GSK ©2021 GSK or licensor

PRINCIPAL DISPLAY PANEL

Advil

MULTI-SYMPTOM
COLD & FLU

Ibuprofen 200 mg Pain Reliever/Fever Reducer (NSAID)
Phenylephrine HCl 10 mg Nasal Decongestant
Chlorpheniramine Maleate 4 mg Antihistamine

- Headache
- Fever
- Body Aches
- Sinus Pressure
- Nasal Congestion
- Runny Nose
- Sneezing
- Nasal Swelling

ONE
TABLET
DOSE!

30Coated Tablets

000065883 Carton